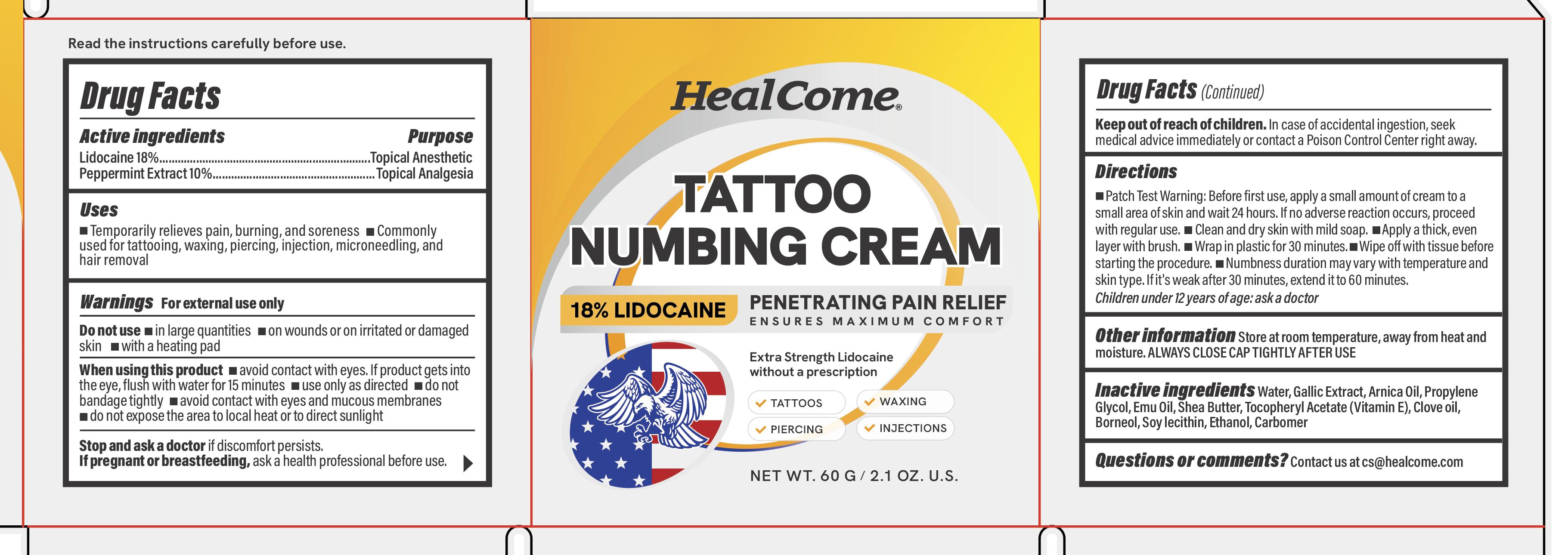 DRUG LABEL: Healcome Tattoo Numbing Cream 18% Lidocaine
NDC: 83364-020 | Form: CREAM
Manufacturer: YITONGBADA (SHENZHEN) INTERNATIONAL TRADE CO., LTD
Category: otc | Type: HUMAN OTC DRUG LABEL
Date: 20250603

ACTIVE INGREDIENTS: LIDOCAINE 18 g/100 g; PEPPERMINT 10 g/100 g
INACTIVE INGREDIENTS: PROPYLENE GLYCOL; CARBOMER 934; .ALPHA.-TOCOPHEROL ACETATE; WATER; BENZYL ALCOHOL; SOYBEAN LECITHIN

Healcome Tattoo Numbing Cream 18% Lidocaine

Drug Facts

Active ingredients

Lidocaine 18%

PURPOSE

Topical Anesthetic

ACTIVE INGREDIENT

Peppermint Extract 10%

PURPOSE

Topical Analgesia

Do not use

- in large quantities - on wounds or on irritated or damaged skin - with a heating pad

When using this product

- avoid contact with eyes. If product gets into the eye, flush with water for 15 minutes - use only as directed - do not bandage tightly - avoid contact with eyes and mucous membranes - do not expose the area to local heat or to direct sunlight

Stop and ask a doctor if discomfort persists.

PREGNANCY OR BREAST FEEDING

If pregnant or breastfeeding, ask a health professional before use.

Keep out of reach of children. In case of accidental ingestion, seek medical advice immediately or contact a Poison Control Center right away.

Uses

- Temporarily relieves pain, burning, and soreness - Commonly used for tattooing, waxing, piercing, injection, microneedling, and hair removal

Warnings

For external use only

Directions

- Patch Test Warning: Before first use, apply a small amount of cream to a small area of skin and wait 24 hours. If no adverse reaction occurs, proceed with regular use. - Clean and dry skin with mild soap. - Apply a thick, even layer with brush. - Wrap in plastic for 30 minutes. - Wipe off with tissue before starting the procedure. - Numbness duration may vary with temperature and skin type. If it's weak after 30 minutes, extend it to 60 minutes.

Children under 12 years of age: ask a doctor

Other information Store at room temperature, away from heat and moisture. ALWAYS CLOSE CAP TIGHTLY AFTER USE

Inactive ingredients
Water, Gallic Extract, Arnica Oil, Propylene Glycol, Emu Oil, Shea Butter, Tocopheryl Acetate (Vitamin E), Clove oil, Borneol, Soy lecithin, Ethanol, Carbomer